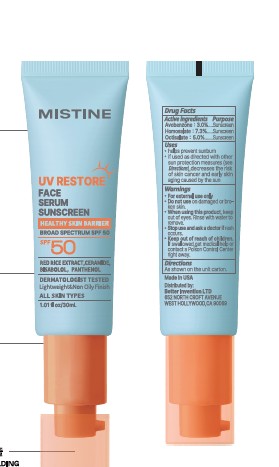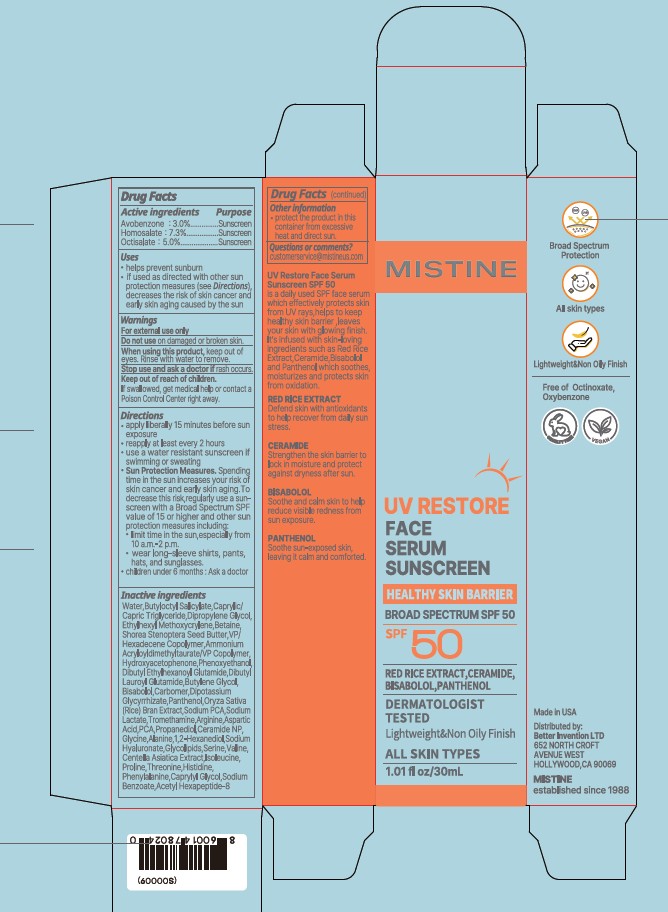 DRUG LABEL: UV RESTORE FACE SERUM SUNSCREEN SPF 50
NDC: 87458-001 | Form: LOTION
Manufacturer: BETTER INNOVATION LTD
Category: otc | Type: HUMAN OTC DRUG LABEL
Date: 20260224

ACTIVE INGREDIENTS: HOMOSALATE 7.3 mg/100 mL; AVOBENZONE 3 mg/100 mL; OCTISALATE 5 mg/100 mL
INACTIVE INGREDIENTS: GLYCINE; ALANINE; ISOLEUCINE; WATER; CAPRYLIC/CAPRIC TRIGLYCERIDE; DIPROPYLENE GLYCOL; ORYZA SATIVA (RICE) BRAN; PANTHENOL; SHOREA STENOPTERA SEED BUTTER; DIBUTYL ETHYLHEXANOYL GLUTAMIDE; VP/HEXADECENE COPOLYMER; PHENOXYETHANOL; CARBOMER; BUTYLOCTYL SALICYLATE; BISABOLOL; CAPRYLYL GLYCOL; SODIUM LACTATE; HISTIDINE; ACETYL HEXAPEPTIDE-8; VALINE; CERAMIDE NP; DIPOTASSIUM GLYCYRRHIZATE; TROMETHAMINE; SODIUM PCA; 1,2-HEXANEDIOL; PROLINE; DIBUTYL LAUROYL GLUTAMIDE; ARGININE; BETAINE; PCA; SERINE; THREONINE; PHENYLALANINE; ETHYLHEXYL METHOXYCRYLENE; HYDROXYACETOPHENONE; PROPANEDIOL; ASPARTIC ACID; CENTELLA ASIATICA TRITERPENOIDS; SODIUM BENZOATE; BUTYLENE GLYCOL; AMMONIUM ACRYLOYLDIMETHYLTAURATE/VP COPOLYMER; SODIUM HYALURONATE

MISTINE UV RESTORE FACE SERUM SUNSCREEN SPF 50

Active ingredients

Avobenzone: 3%

Homosalate: 7.3%

Octisalate: 5.0%

Purpose

Sunscreen

USES

- help prevent sunburn
- if used as directed with other sun protection measures (see Directions), decreases the risk of skin cancer and early skin aging caused by the sun

Warnings

For external use only

Do not use on damaged or broken skin

When using this product, keep out of eyes. Rinse with water to remove.

Stop use and ask a doctor if rash occurs.

Keep out of reach of children. If swallowed, get medical help or contact a Poison Control Center right away.

DIRECTIONS

- apply liberally 15 minutes before sun exposure
- reapply at least every 2 hours
- use a water resistant sunscreen if swimming or sweating
- Sun Protection Measures. Spending time in the sun increases your risk of skin cancer and early skin aging.To decrease this risk, regularly use a sunscreen with a Broad Spectrum SPF value of 15 or higher and other sun protection measures including:
- limit time in the sun, especially from 10 a.m.- 2 p.m.
- wear long-sleeve shirts, pants, hats, and sunglasses.
- children under 6 months: Ask doctor

Inactive ingredients

Water, Butyloctyl Salicylate, Caprylic/Capric Triglyceride, Dripropylene Glycol, Ethylhexyl Methoxycrylene, Betaine, Shorea Stenoptera Seed Butter, VP/Hexadecene Copolymer, Ammonium Acryloyldimethyltaurate/VP Copolymer, Hydroxyacetophenone, Phenoxyethanol, Dibutyl Ethylhexanoyl Glutamide, Dibutyl Lauroyl Glutamide, Butylene Glycol, Bisabolol, Carbomer, Dipotassium Glycyrrhizate, Panthenol, Oryza Sativa (Rice) Bran Extract, Sodium PCA, Sodium Lactate, Tromethamine, Arginine, Aspartic Acid, PCA, Propanediol, Ceramide NP, Glycine, Alanine, 1,2-Hexanediol, Sodium Hyaluronate, Glycolipids, Serine, Valine, Centella Asiatica Extract, Isoleucine, Proline, Threonine, Histidine, Phenylalanine, Caprylyl Glycol, Sodium Benzoate, Acetyl Hexapeptide-8.

OTHER INFORMATION

- protect the product in this container from excessive heat and direct sun

QUESTIONS OR COMMENTS

customerservice@mistineus.com